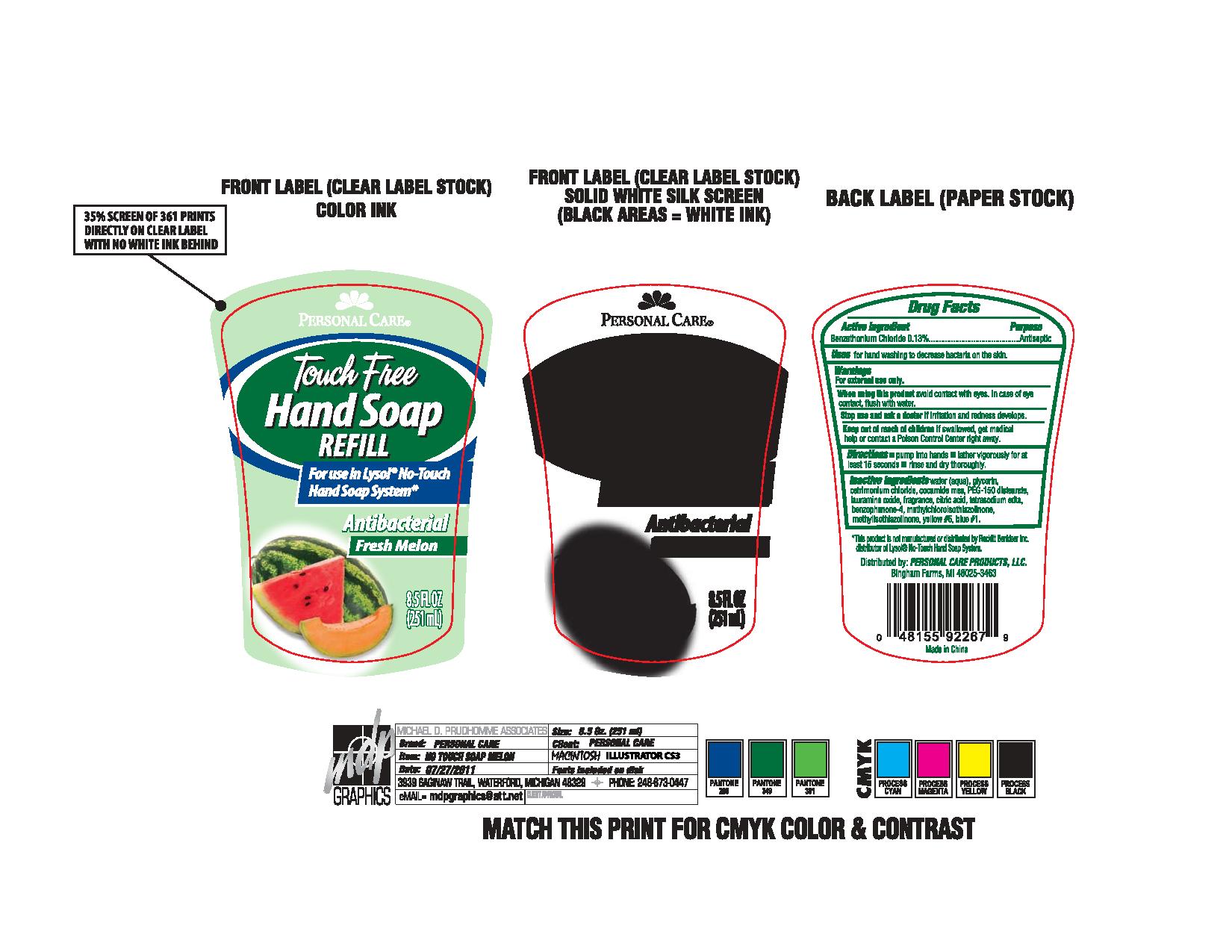 DRUG LABEL: Touch Free Hand
NDC: 29500-9711 | Form: SOAP
Manufacturer: Personal Care Products
Category: otc | Type: HUMAN OTC DRUG LABEL
Date: 20110729

ACTIVE INGREDIENTS: benzethonium chloride .33 mL/251 mL
INACTIVE INGREDIENTS: WATER; GLYCERIN; CETRIMONIUM CHLORIDE; COCO MONOETHANOLAMIDE; PEG-150 DISTEARATE; LAURAMINE OXIDE; CITRIC ACID; EDETATE SODIUM; METHYLCHLOROISOTHIAZOLINONE; METHYLISOTHIAZOLINONE; FD&C YELLOW NO. 5; FD&C BLUE NO. 1

touch free hand

Active Ingredient benzethonium chloride

Purpose Antiseptic

Keep out of reach of children If swallowed, get medical help or contact a Poison Control Center right away.

INDICATIONS AND USAGE

Uses for hand washing to decrease bacteria on the skin.

Warnings

For external use only.

When using this product avoid contact with eyes. In case of eye contact, flush with water.

Stop use and ask a doctor if irritation and redness develops.

Directions

pump into hands

lather vigorously for at least 15 seconds

Rinse and dry thoroughly

Inactive ingredients
water (aqua), glycerin, cerimonium chloride, cocamide mea, PEG-150 distearate, lauramine oxide, fragrance, citric acid, tetrasodium edta, benzophenone-4, methylchloroisothiazolinone, methylisothiazolinone, yellow #5, blue #1.

PACKAGE LABEL

Personal Care

Touch Free Hand Soap Refill

For use in Lysol No Touch Hand Soap System

Antibacterial

Fresh Melon

8.5 fl oz

(251 ml)